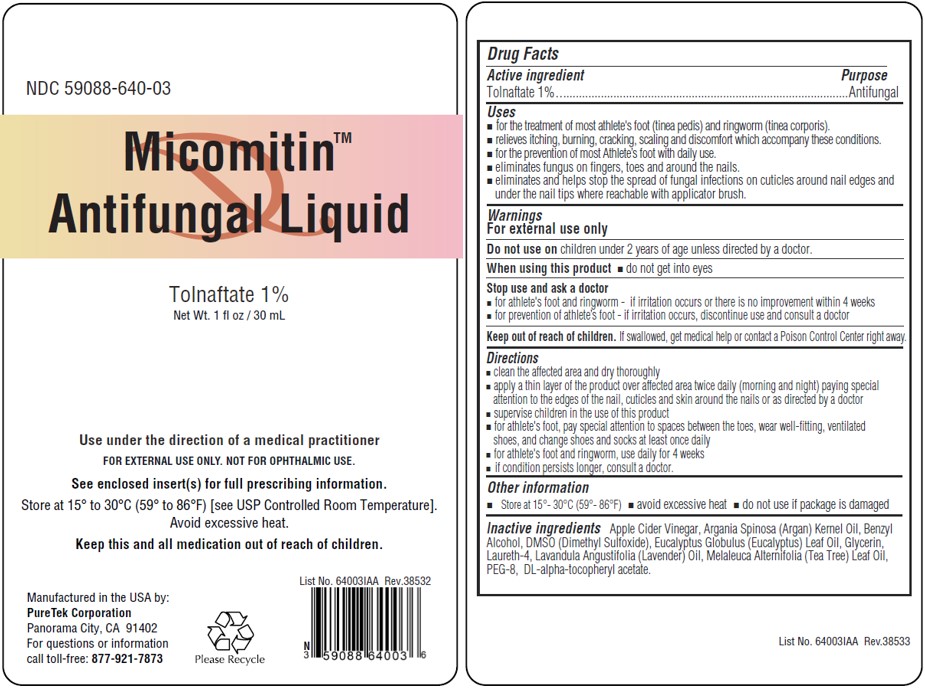 DRUG LABEL: Micomitin Antifungal
NDC: 59088-640 | Form: LIQUID
Manufacturer: PureTek Corporation
Category: otc | Type: HUMAN OTC DRUG LABEL
Date: 20241016

ACTIVE INGREDIENTS: TOLNAFTATE 0.3 g/30 mL
INACTIVE INGREDIENTS: ARGAN OIL; BENZYL ALCOHOL; .ALPHA.-TOCOPHEROL ACETATE, DL-; DIMETHYL SULFOXIDE; EUCALYPTUS OIL; GLYCERIN; LAURETH-4; LAVENDER OIL; TEA TREE OIL; POLYETHYLENE GLYCOL 400; APPLE CIDER VINEGAR

Micomitin™
Antifungal Liquid
Tolnaftate 1%

Active ingredient

Tolnaftate 1%

Purpose

Antifungal

Uses

- for the treatment of most athlete's foot (tinea pedis) and ringworm (tinea corporis).
- relieves itching, burning, cracking, scaling, and discomfort which accompany these conditions.
- for the prevention of most Athlete’s foot with daily use.
- eliminates fungus on fingers, toes, and around the nails.
- eliminates and helps stop the spread of fungal infections on cuticles around nail edges and under the nail tips where reachable with applicator brush.

Warnings

For external use only

Do not use on

children under 2 years of age unless directed by a doctor.

When using this product

- do not get into eyes

Stop use and ask a doctor

- for athlete's foot and ringworm - if irritation occurs or there is no improvement within 4 weeks
- for prevention of athlete’s foot - if irritation occurs, discontinue use and consult a doctor

Keep out of reach of children.

If swallowed, get medical help or contact a Poison Control Center right away.

Directions

- clean the affected area and dry thoroughly
- apply a thin layer of the product over affected area twice daily (morning and night) paying special attention to the edges of the nail, cuticles, and skin around the nails or as directed by a doctor
- supervise children in the use of this product
- for athlete's foot, pay special attention to spaces between the toes, wear well-fitting, ventilated shoes, and change shoes and socks at least once daily
- for athlete's foot and ringworm, use daily for 4 weeks
- if condition persists longer, consult a doctor.

Use under the direction of a medical practitioner

Other information

- Store at 15 - 30°C (59° - 86°F) [see USP Controlled Room Temperature].
- avoid excessive heat
- do not use if package is damaged

How Supplied

Micomitin™ Antifungal Liquidis supplied in a 1 fl oz / 30 mL glass bottle with a screw cap fitted with a brush applicator (NDC 59088-640-03)

Inactive ingredients

Apple Cider Vinegar, Argania Spinosa (Argan) Kernel Oil, Benzyl Alcohol, DMSO (Dimethyl Sulfoxide), Eucalyptus Globulus (Eucalyptus) Leaf Oil, Glycerin, Laureth-4, Lavandula Angustifolia (Lavender) Oil, Melaleuca Alternifolia (Tea Tree) Leaf Oil, PEG-8, DL-alpha-tocopheryl acetate.

Micomitin™ Antifungal Liquid

Manufactured in the USA by:
PureTek Corporation
Panorama City, CA 91402
For questions or information
call toll-free: 877-921-7873